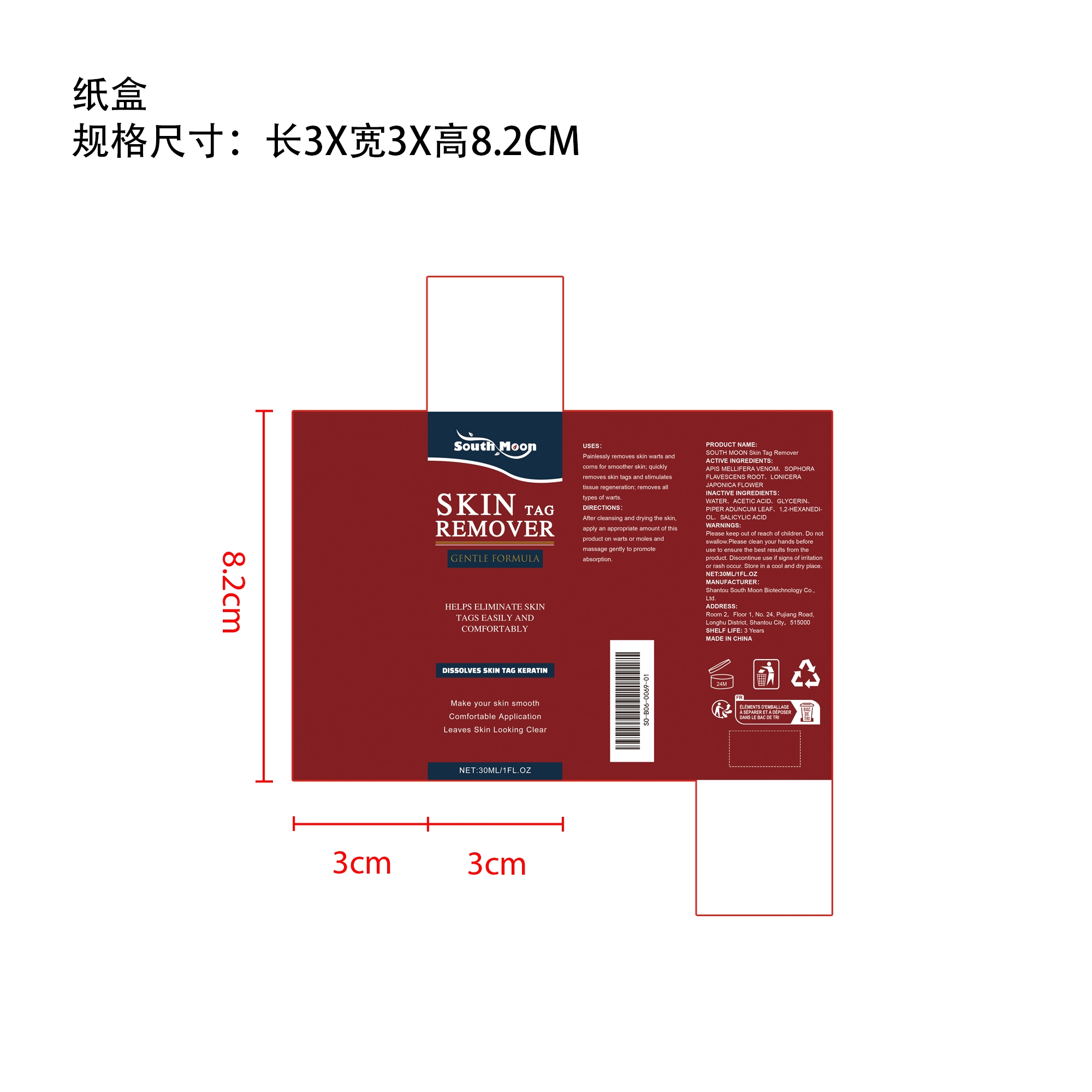 DRUG LABEL: SOUTH MOON Skin Tag Remover
NDC: 84983-012 | Form: LIQUID
Manufacturer: Shantou South Moon Biotechnology Co., Ltd.
Category: otc | Type: HUMAN OTC DRUG LABEL
Date: 20251127

ACTIVE INGREDIENTS: LONICERA JAPONICA FLOWER 0.03 mg/30 mg; SOPHORA FLAVESCENS ROOT 0.03 mg/30 mg; APIS MELLIFERA VENOM 0.03 mg/30 mg
INACTIVE INGREDIENTS: 1,2-HEXANEDIOL 0.15 mg/30 mg; ACETIC ACID 1.5 mg/30 mg; SALICYLIC ACID 0.03 mg/30 mg; GLYCERIN 0.6 mg/30 mg; PIPER ADUNCUM LEAF 0.6 mg/30 mg; WATER 27.03 mg/30 mg

ACTIVE INGREDIENT

APIS MELLIFERA VENOM、SOPHORA FLAVESCENS ROOT、LONICERA JAPONICA FLOWER

WHEN USING

After cleansing and drying the skin, apply an appropriate amount of this product on warts or moles and massage gently to promote absorption.

PURPOSE

Painlessly removes skin warts and corns for smoother skin; quickly removes skin tags and stimulates tissue regeneration; removes all types of warts.

WARNINGS

Please keep out of reach of children. Do not swallow.Please clean your hands before use to ensure the best results from the product. Discontinue use if signs of irritation or rash occur. Store in a cool and dry place.

DO NOT USE

Discontinue use if signs of irritation or rash occur.

STOP USE

Discontinue use if signs of irritation or rash occur.

KEEP OUT OF REACH OF CHILDREN

Please keep out of reach of children. Do not swallow.

STORAGE AND HANDLING

Store in a cool and dry place.

INACTIVE INGREDIENT

WATER、ACETIC ACID、GLYCERIN、PIPER ADUNCUM LEAF、1,2-HEXANEDIOL、SALICYLIC ACID

DOSAGE AND ADMINISTRATION

After cleansing and drying the skin, apply an appropriate amount of this product on warts or moles and massage gently to promote absorption.

INDICATIONS AND USAGE

Painlessly removes skin warts and corns for smoother skin; quickly removes skin tags and stimulates tissue regeneration; removes all types of warts.